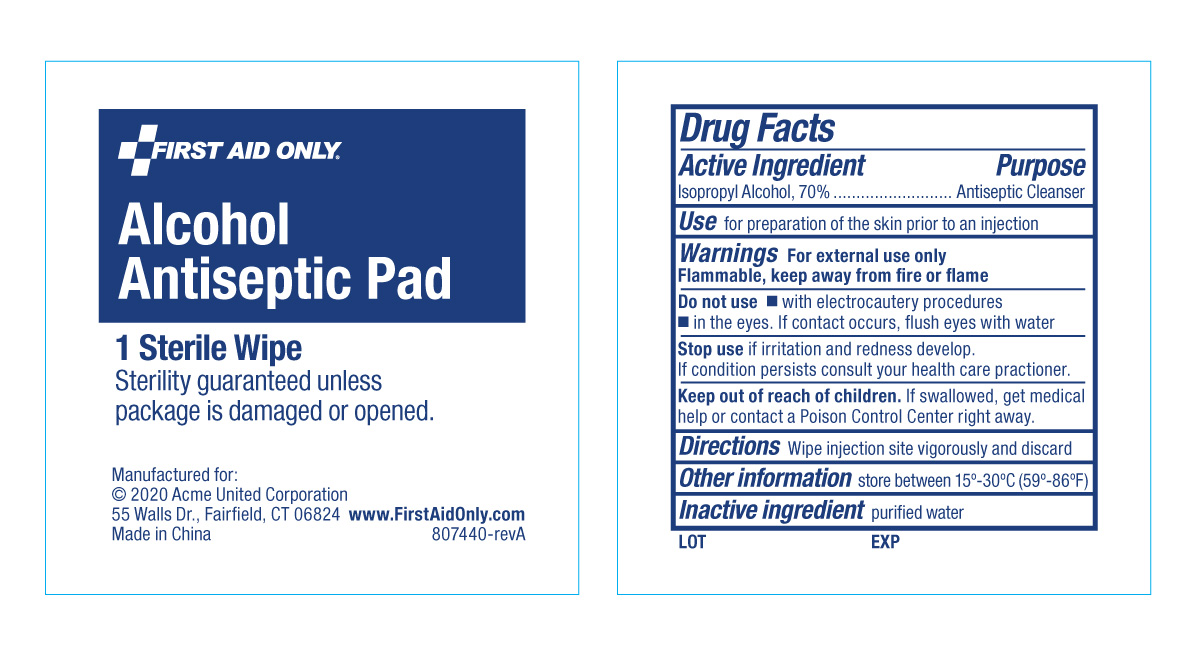 DRUG LABEL: First Aid Only Alcohol Antiseptic
NDC: 0924-0017 | Form: LIQUID
Manufacturer: Acme United Corporation
Category: otc | Type: HUMAN OTC DRUG LABEL
Date: 20241123

ACTIVE INGREDIENTS: ISOPROPYL ALCOHOL 70 mL/100 mL
INACTIVE INGREDIENTS: WATER

First Aid Only Alcohol Antiseptic Pad

Active ingredient

Isopropyl Alcohol, 70% v/v

Purpose

Antiseptic Cleanser

Use

For preparation of the skin prior to an injection.

Warnings

For external use only. Flammable, keep away from fire or flame.

Do not use

- with electrocautery procedures
- in the eyes. If contact occurs, flush eyes with water

Stop use

if irritation and redness develop. . If condition persists consult your health care practitioner.

Keep out of reach of children.

If swallowed, get medical help or contact a Poison Control center right away.

Directions

- Wipe injection site vigorously and discard.

Other information

- Store at room temperature 15 - 30°C (59 - 86°F)

Inactive ingredient

Purified Water